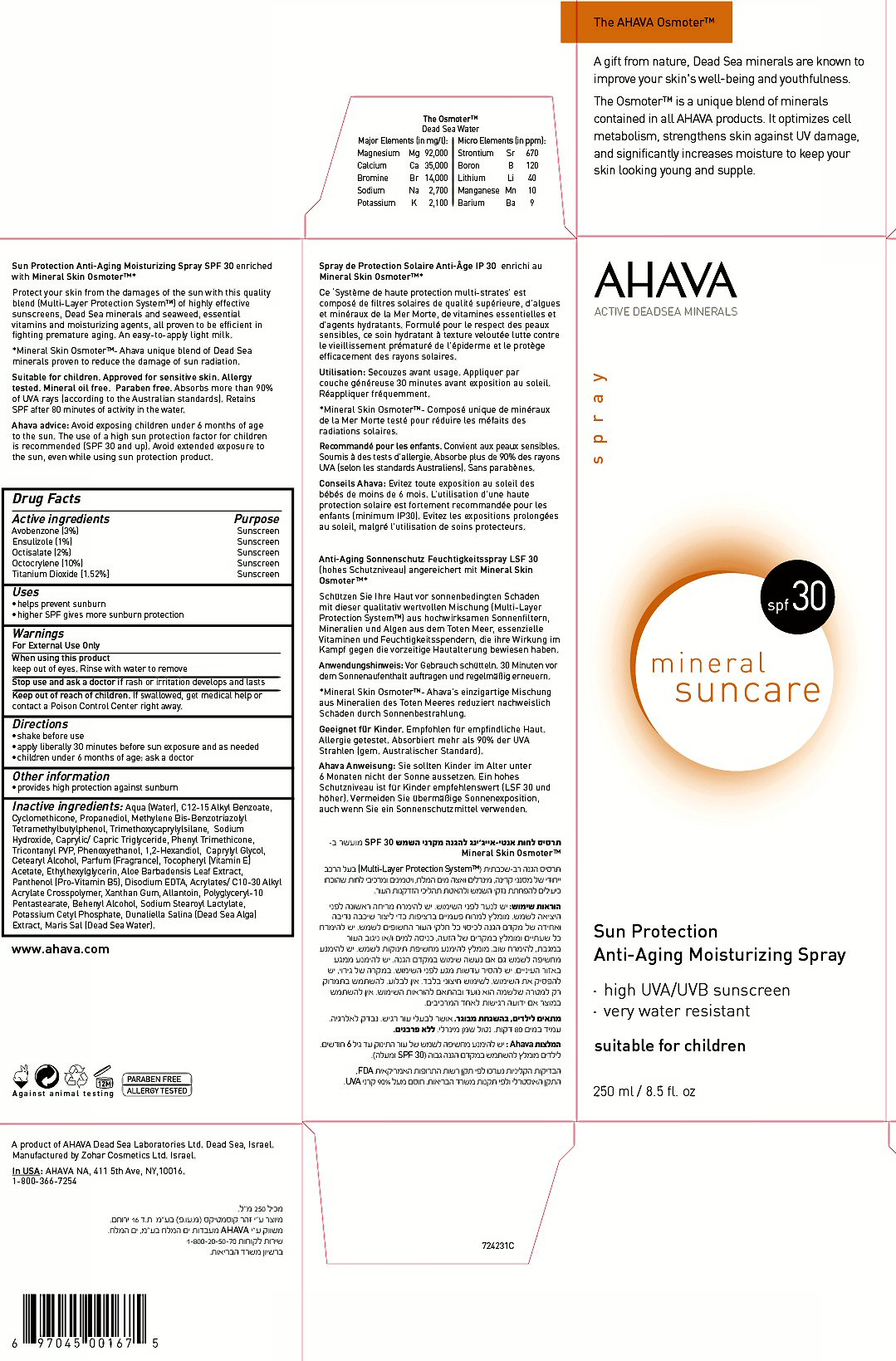 DRUG LABEL: AHAVA ACTIVE DEADSEA MINERALS
NDC: 60289-030 | Form: SPRAY
Manufacturer: AHAVA - Dead Sea Laboratories Ltd.
Category: otc | Type: HUMAN OTC DRUG LABEL
Date: 20120222

ACTIVE INGREDIENTS: OCTOCRYLENE 25 mL/250 mL; ENSULIZOLE 2.5 mL/250 mL; OCTISALATE 5 mL/250 mL; AVOBENZONE 7.5 mL/250 mL; TITANIUM DIOXIDE 3.8 mL/250 mL
INACTIVE INGREDIENTS: WATER; ALKYL (C12-15) BENZOATE; CYCLOMETHICONE; PROPANEDIOL; BISOCTRIZOLE; TRIMETHOXYCAPRYLYLSILANE; SODIUM HYDROXIDE; MEDIUM-CHAIN TRIGLYCERIDES; PHENYL TRIMETHICONE; TRIACONTANYL PVP (WP-660); PHENOXYETHANOL; 1,2-HEXANEDIOL; CAPRYLYL GLYCOL; CETOSTEARYL ALCOHOL; ALPHA-TOCOPHEROL ACETATE; ETHYLHEXYLGLYCERIN; ALOE VERA LEAF; PANTHENOL; EDETATE DISODIUM; CARBOMER INTERPOLYMER TYPE A (55000 MPA.S) ; XANTHAN GUM; ALLANTOIN; POLYGLYCERYL-10 OLEATE; DOCOSANOL; SODIUM STEAROYL LACTYLATE; POTASSIUM CETYL PHOSPHATE; DUNALIELLA SALINA; MAGNESIUM; CALCIUM; BROMINE; SODIUM; POTASSIUM; STRONTIUM; BORON; LITHIUM; MANGANESE; BARIUM

Active Ingredient Section

Drug Facts
Active Ingredients Avobenzone (3%) Ensulizole (1%) Octisalate (2%) Octocrylene (10%) Titanium Dioxide (1.52%)

Purpose Section

Purpose Sunscreen

Keep Out of reach of Children Section

Keep out of reach of children. If swallowed, get medical help or contact a Poison Control Center right away.

Uses Section

Uses
* helps prevent sunburn
* higher SPF gives more sunburn protection

Warnings Section

Warnings
For External Use Only When using this product keep out of eyes. Rinse with water to remove
Stop use and ask a doctor if rash or irritation develops and lasts If swallowed, get medical help or contact a Poison Control Center right away.

Directions Section

Directions
* shake before using
* apply liberally 30 minutes before sun exposure and as needed
* children under 6 months of age: ask a doctor

Inactive Ingredient Section

Inactive ingredients: Aqua (Water), C12-15 Alkyl Benzoate, Cyclomethicone, Propanediol, Methylene Bis-Benzotriazolyl Tetramethtbutylphenol, Trimethoxycaprlylsilane, Sodium Hydroxide, Caprylic/Capric Triglyceride, Phenyl Trimethicone, Tricontanyl PVP, Phenoxyethanol, 1,2-Hexandiol, Caprylyl Glycol, Cetearyl Alcohol, Parfum (Fragrance), Tocopheryl (Vitamin E) Acetate, Ethylhexylglycerin, Aloe Barbadensis Leaf Extract, Panthenol (Pro-Vitamin B5), Disodium EDTA, Acrylates/ C10-30 Alkyl Acrylate Crosspolymer, Xanthan Gum, Allantoin, Polyglyceryl-10 Pentastearate, Behenyl Alcohol, Sodium Stearoyl Lactylate, Potassium Cetyl Phosphate, Dunalietta Salina (Dead Sea Alga) Extract, Maris Sal (Dead Sea Water)
The Osmotertm Dead Sea Water
Major Elements /in mg/L: Micro Elements /in ppml:
Magnesium Mg 92,000 Stronium Sr 670
Calcium Ca 35,000 Boron B 120
Bromine Br 14,000 Lithium Li 40
Sodium Na 2,700 Manganese Mn 10
Potassium K 2,100 Barium Ba 9

Other information Section

Other information
* provides moderate protection against sunburn

Package Label

The AHAVA Osmoter tm A gift from nature, Dead Sea minerals are known to improve your skin's well-being and youthfulness.
The osmoter tm is a unique blend of minerals contained in all AHAVA products. It optimizes cell metabolism, strenghtens skin against UV damage, and significantly increases moisture to keep your skin looking young and supple.
AHAVA ACTIVE DEAD SEA MINERALS SPRAY spf 30 mineral SUNCARE
Sun Protection Anti-Aging Moisturizing Spray
* moderate UVA/UVB sunscreen
* very water resistant

suitable for children

250 ml / 8.5 fl. oz
Sun protection Anti-Aging moisturizing Spray SPF 30 enriched with Mineral Skin Osmoter tm
Protect your skin from the damages of the sun with this quality blend (Multi-Layer Protection System tm) of highly effective sunscreens. Dead Sea minerals and seaweed, essential vitamins and moisturizing agents, all proven to be efficient in fighting premature aging. An easy-to-apply light milk.
* Mineral Skin Osmoter tm - Ahava unique blend of Dead Sea minerals proven to reduce the damage of sun radiation.
Suitable for children. Approved for sensitive skin. Allergy tested. Mineral oil free. Paraben free. Absorbs more than 90% of UVA rays (according to the Australian standards). Retains SPF after 80 minutes of activity in the water.
Ahava advice: Avoid exposing children under 6 months of age to the sun. The use of a high sun protection factor for children is recommended (SPF 30 and up). Avoid extended exposure to the sun, even while using this product.
www.ahava.com
Against animal testing PARABEN FREE ALLERGY TESTED
A product of AHAVA Dead Sea Laboratories, Ltd. Dead Sea, israel. Manufactures by Zohar Cosmetics Ltd. POB 16 Yerucham, israel.
In USA: Ahava NA, 411 5th Ave. NY, 10016 1-800-366-7254